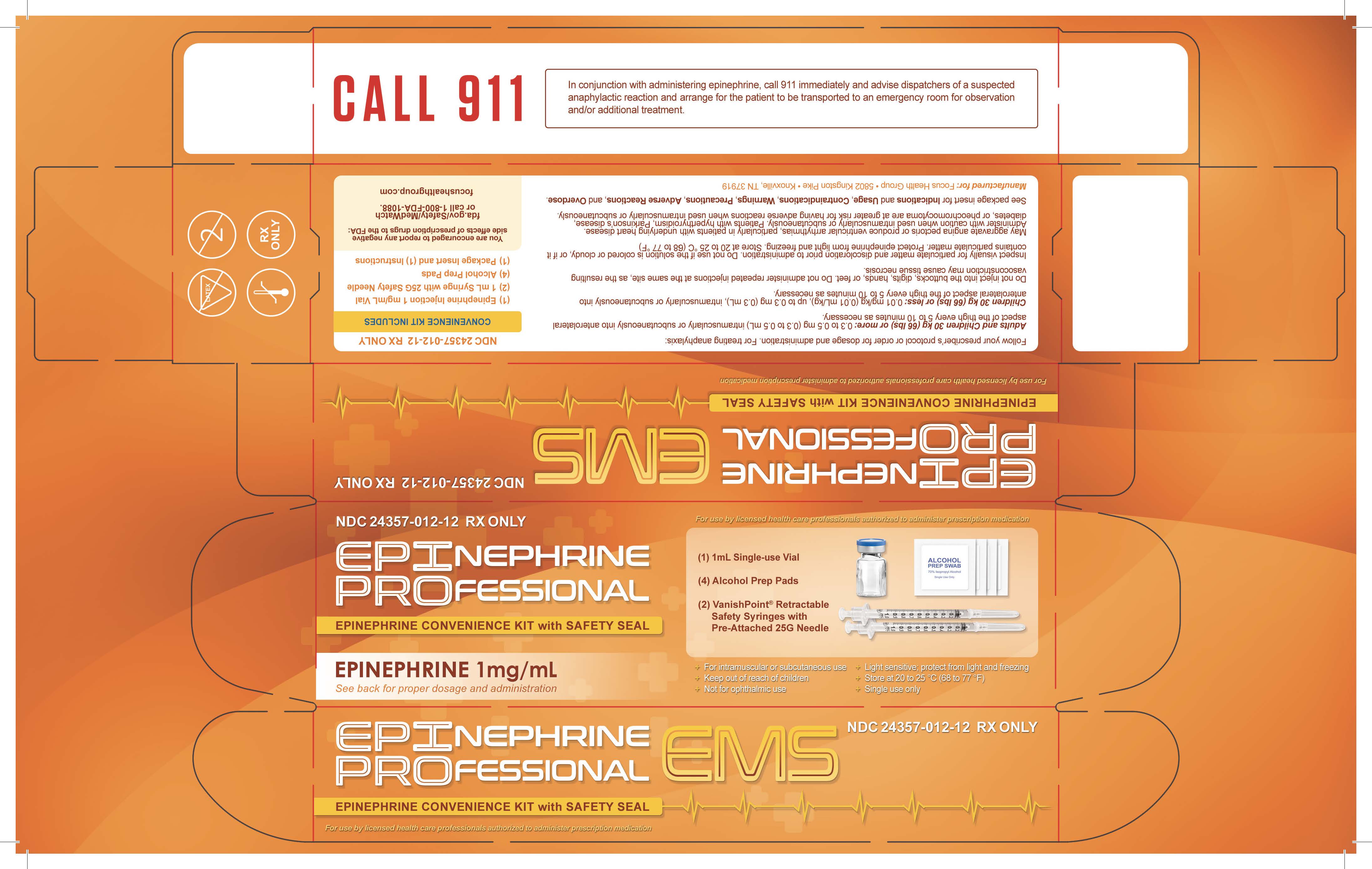 DRUG LABEL: Epinephrine Professional EMS
NDC: 24357-012 | Form: KIT | Route: INTRAMUSCULAR
Manufacturer: Focus Health Group
Category: prescription | Type: HUMAN PRESCRIPTION DRUG LABEL
Date: 20230410

ACTIVE INGREDIENTS: EPINEPHRINE 1 mg/1 mL; ISOPROPYL ALCOHOL 0.7 mL/1 mL
INACTIVE INGREDIENTS: SODIUM METABISULFITE 0.457 mg/1 mL; TARTARIC ACID 2.25 mg/1 mL; SODIUM HYDROXIDE 1 mg/1 mL; HYDROCHLORIC ACID; SODIUM CHLORIDE 7.3 mg/1 mL; WATER; EDETATE DISODIUM 0.2 mg/1 mL; WATER

Epinephrine Professional EMS Conenience Kit

Dosage and Administration:

Always follow the prescriber’s order for dosing and administration.

Adrenamine may be administered for anaphylaxis:

o Adults and Children 30 kg (66 lbs) or more: 0.3 to 0.5 mg (0.3 to 0.5 mL) intramuscularly or subcutaneously into anterolateral aspect of the thigh every 5 to 10 minutes as necessary

o Children 30 kg (66 lbs) or less: 0.01 mg/kg (0.01 mL/kg), up to 0.3 mg (0.3 mL), intramuscularly or subcutaneously into anterolateral aspect of the thigh every 5 to 10 minutes as necessary